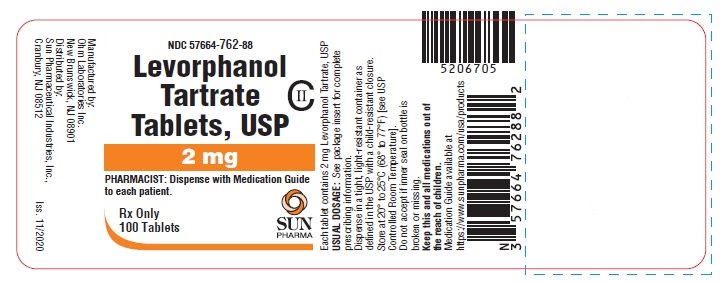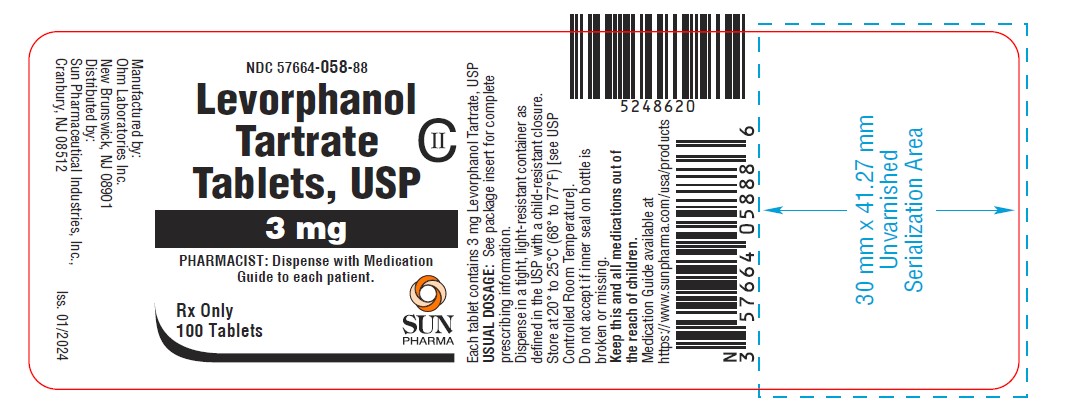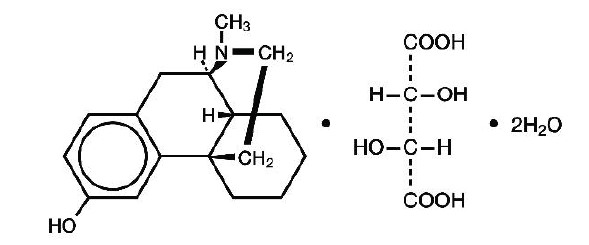 DRUG LABEL: Levorphanol Tartrate
NDC: 57664-762 | Form: TABLET
Manufacturer: Sun Pharmaceutical Industries, Inc.
Category: prescription | Type: HUMAN PRESCRIPTION DRUG LABEL
Date: 20260113
DEA Schedule: CII

ACTIVE INGREDIENTS: LEVORPHANOL TARTRATE 2 mg/1 1
INACTIVE INGREDIENTS: MICROCRYSTALLINE CELLULOSE; ANHYDROUS LACTOSE; STARCH, CORN; MAGNESIUM STEARATE

Levorphanol Tartrate Tablets USP, CII

WARNING: SERIOUS AND LIFE-THREATENING RISKS FROM USE OF LEVORPHANOL TARTRATE TABLETS

Addiction, Abuse, and Misuse

Because the use of levorphanol tartrate tablets exposes patients and other users to the risks of opioid addiction, abuse, and misuse, which can lead to overdose and death, assess each patient’s risk prior to prescribing and reassess all patients regularly for the development of these behaviors and conditions [see WARNINGS] .

Life-Threatening Respiratory Depression

Serious, life-threatening, or fatal respiratory depression may occur with use of levorphanol tartrate tablets, especially during initiation or following a dosage increase. To reduce the risk of respiratory depression, proper dosing and titration of levorphanol tartrate tablets are essential [see WARNINGS] .

Accidental Ingestion

Accidental ingestion of even one dose of levorphanol tartrate tablets, especially by children, can result in a fatal overdose of levorphanol [see WARNINGS] .

Risks From Concomitant Use With Benzodiazepines Or Other CNS Depressants

Concomitant use of opioids with benzodiazepines or other central nervous system (CNS) depressants, including alcohol, may result in profound sedation, respiratory depression, coma, and death. Reserve concomitant prescribing of levorphanol tartrate tablets and benzodiazepines or other CNS depressants for use in patients for whom alternative treatment options are inadequate [see WARNINGS].

Neonatal Opioid Withdrawal Syndrome (NOWS)

Advise pregnant women using opioids for an extended period of time of the risk of Neonatal Opioid Withdrawal Syndrome, which may be life-threatening if not recognized and treated. Ensure that management by neonatology experts will be available at delivery [see WARNINGS].

Opioid Analgesic Risk Evaluation and Mitigation Strategy (REMS)

- Healthcare providers are strongly encouraged to complete a REMS-compliant education program and to counsel patients and caregivers on serious risks, safe use, and the importance of reading the Medication Guide with each prescription [see WARNINGS] .

DESCRIPTION

Levorphanol tartrate tablets USP, contain levorphanol, an opioid agonist with a molecular formula of C17H23NO • C4H6O6• 2H2O and molecular weight 443.5. Each milligram of levorphanol tartrate is equivalent to 0.58 mg levorphanol base. Levorphanol's chemical name is levo-3-hydroxy-N-methylmorphinan. The USP nomenclature is 17- methylmorphinan 3-ol tartrate (1:1) (Salt) dihydrate. The material has 3 asymmetric carbon atoms. The chemical structure is:

Levorphanol tartrate, USP is a white crystalline powder, soluble in water and ether, but insoluble in chloroform.

Levorphanol tartrate tablets, USP, for oral administration, are available in two strengths:

2 mg tablet: white to off-white, flat face beveled edge tablet, bisect scored on one side and debossed with “762” on other side.

3 mg tablet: white to off-white, oval tablet, debossed with “058” on one side.

In addition, each tablet contains microcrystalline cellulose, anhydrous lactose, pregelatinized starch, and magnesium stearate.

CLINICAL PHARMACOLOGY

Mechanism of Action

Levorphanol is a full opioid agonist and is relatively selective for the mu-opioid receptor, although it can bind to other opioid receptors at higher doses. The principal therapeutic action of levorphanol is analgesia. Like all full opioid agonists, there is no ceiling effect for analgesia with levorphanol. Clinically, dosage is titrated to provide adequate analgesia and may be limited by adverse reactions, including respiratory and CNS depression.

The precise mechanism of the analgesic action is unknown. However, specific CNS opioid receptors for endogenous compounds with opioid-like activity have been identified throughout the brain and spinal cord and are thought to play a role in the analgesic effects of this drug.

Pharmacodynamics

Effects on the Central Nervous System

The principal therapeutic action of levorphanol is analgesia.

Levorphanol produces respiratory depression by direct action on brain stem respiratory centers. The respiratory depression involves a reduction in the responsiveness of the brain stem respiratory centers to both increases in carbon dioxide retention and electrical stimulation.

Levorphanol causes miosis, even in total darkness. Pinpoint pupils are a sign of opioid overdose but are not pathognomonic (e.g., pontine lesions of hemorrhagic or ischemic origins may produce similar findings). Marked mydriasis rather than miosis may be seen due to hypoxia in overdose situations.

Effects on the Gastrointestinal Tract and Other Smooth Muscle

Levorphanol causes a reduction in motility associated with an increase in smooth muscle tone in the antrum of the stomach and duodenum. Digestion of food in the small intestine is delayed and propulsive contractions are decreased. Propulsive peristaltic waves in the colon are decreased, while tone may be increased to the point of spasm, resulting in constipation. Other opioid-induced effects may include a reduction in biliary and pancreatic secretions, spasm of sphincter of Oddi, transient elevations in serum amylase, and opioid-induced esophageal dysfunction (OIED) .

Effects on the Cardiovascular System

Levorphanol produces peripheral vasodilation which may result in orthostatic hypotension or syncope. Manifestations of histamine release and/or peripheral vasodilation may include pruritus, flushing, red eyes, sweating, and/or orthostatic hypotension.

Effects on the Endocrine System

Opioids inhibit the secretion of adrenocorticotropic hormone (ACTH), cortisol, and luteinizing hormone (LH) in humans [see ADVERSE REACTIONS]. They also stimulate prolactin, growth hormone (GH) secretion, and pancreatic secretion of insulin and glucagon.

Use of opioids for an extended period of time may influence the hypothalamic-pituitary-gonadal axis, leading to androgen deficiency that may manifest as low libido, impotence, erectile dysfunction, amenorrhea, or infertility. The causal role of opioids in the clinical syndrome of hypogonadism is unknown because the various medical, physical, lifestyle, and psychological stressors that may influence gonadal hormone levels have not been adequately controlled for in studies conducted to date [see ADVERSE REACTIONS].

Effects on the Immune System

Opioids have been shown to have a variety of effects on components of the immune system. The clinical significance of these findings is unknown. Overall, the effects of opioids appear to be modestly immunosuppressive.

Concentration–Efficacy Relationships

The minimum effective analgesic concentration will vary widely among patients, especially among patients who have been previously treated with opioid agonists. The minimum effective analgesic concentration of levorphanol for any individual patient may increase over time due to an increase in pain, the development of a new pain syndrome, and/or the development of analgesic tolerance [see DOSAGE AND ADMINISTRATION].

Concentration–Adverse Reaction Relationships

There is a relationship between increasing levorphanol plasma concentration and increasing frequency of dose-related opioid adverse reactions such as nausea, vomiting, CNS effects, and respiratory depression. In opioid-tolerant patients, the situation may be altered by the development of tolerance to opioid-related adverse reactions [see DOSAGE AND ADMINISTRATION].

Pharmacokinetics

The pharmacokinetics of levorphanol have been studied in a limited number of cancer patients following intravenous (IV), intramuscular (IM) and oral (PO) administration. Following IV administration plasma concentrations of levorphanol decline in a triexponential manner with a terminal half-life of 11 to 16 hours and a clearance of 0.78 to 1.1 L/kg/hr. Based on terminal half-life, steady-state plasma concentrations should be achieved by the third day of dosing.

Levorphanol is rapidly distributed (<1 hr) and redistributed (1 to 2 hours) following IV administration and has a steady-state volume of distribution of 10 to 13 L/kg. In vitrostudies of protein binding indicate that levorphanol is only 40% bound to plasma proteins.

No pharmacokinetic studies of the absorption of IM levorphanol are available, but clinical data suggests that absorption is rapid with onset of effects within 15 to 30 minutes of administration.

Levorphanol is well absorbed after PO administration with peak plasma concentrations occurring approximately 1 hour after dosing. The bioavailability of levorphanol tartrate tablets compared to IM or IV administration is not known.

Plasma concentrations of levorphanol following chronic administration in patients with cancer increased with the dose, but the analgesic effect was dependent on the degree of opioid tolerance of the patient. Expected steady-state plasma concentrations for a 6-hour dosing interval can reach 2 to 5 times those following a single dose, depending on the patient's individual clearance of the drug. Very high plasma concentrations of levorphanol can be reached in patients on chronic therapy due to the long half-life of the drug. One study in 11 patients using the drug for control of cancer pain reported plasma concentrations from 5 to 10 ng/mL after a single 2 mg dose and up to 50 to 100 ng/mL after repeated oral doses of 20 to 50 mg/day.

Animal studies suggest that levorphanol is extensively metabolized in the liver and is eliminated as the glucuronide metabolite. This renally excreted inactive glucuronide metabolite accumulates with chronic dosing in plasma at concentrations that reach fivefold that of the parent compound.

The effects of age, sex, hepatic and renal disease on the pharmacokinetics of levorphanol are not known. As with all drugs of this class, patients at the extremes of age are expected to be more susceptible to adverse effects because of a greater pharmacodynamic sensitivity and probable increased variability in pharmacokinetics due to age or disease.

Clinical Trials

Clinical trials have been reported in the medical literature that investigated the use of levorphanol tartrate tablets as a preoperative medication, as a postoperative analgesic, and in the management of chronic pain due primarily to malignancy. In each of these clinical settings levorphanol tartrate tablets has been shown to be an effective analgesic of the mu-opioid type and similar to morphine, meperidine, or fentanyl.

Levorphanol tartrate tablets have been studied in chronic cancer patients. Dosages were individualized to each patient's level of opioid tolerance. In one study, starting doses of 2 mg twice a day often had to be advanced by 50% or more within a few weeks of starting therapy. A study of levorphanol tartrate tablets indicates that the relative potency is approximately 4 to 8 times that of morphine, depending on the specific circumstances of use. In postoperative patients, intramuscular levorphanol was determined to be about 8 times as potent as intramuscular morphine, whereas in cancer patients with chronic pain, it was found only to be about 4 times as potent.

Individualization of Dosage

Accepted medical practice dictates that the dose of any opioid analgesic be appropriate to the degree of pain to be relieved, the clinical setting, the physical condition of the patient, and the kind and dose of concurrent medication.

Levorphanol has a long half-life similar to methadone or other slowly excreted opioids, rather than quickly excreted agents such as morphine or meperidine. Slowly excreted drugs may have some advantages in the management of chronic pain. Unfortunately, the duration of pain relief after a single dose of a slowly excreted opioid cannot always be predicted from pharmacokinetic principles, and the inter-dose interval may have to be adjusted to suit the patient's individual pharmacodynamic response.

Levorphanol is 4 to 8 times as potent as morphine and has a longer half-life. Because there is incomplete cross-tolerance among opioids, when converting a patient from morphine to levorphanol, the total dailydose of oral levorphanol should begin at approximately 1/15 to 1/12 of the total dailydose of oral morphine that such patients had previously required and then the dose should be adjusted to the patient's clinical response. If a patient is to be placed on fixed-schedule dosing (round-the-clock) with this drug, care should be taken to allow adequate time after each dose change (approximately 72 hours) for the patient to reach a new steady-state before a subsequent dose adjustment to avoid excessive sedation due to drug accumulation.

INDICATIONS AND USAGE

Levorphanol tartrate tablets are indicated for the management of pain severe enough to require an opioid analgesic and for which alternative treatments are inadequate.

Limitations of Use

Because of the risks of addiction, abuse, misuse, overdose, and death which can occur at any dosage or duration, and persist over the course of therapy [see WARNINGS], reserve opioid analgesics, including levorphanol tartrate tablets, for use in patients for whom alternative treatment options are ineffective, not tolerated, or would be otherwise inadequate to provide sufficient management of pain.

CONTRAINDICATIONS

Levorphanol tartrate tablets are contraindicated in patients with:

- Significant respiratory depression [see WARNINGS]
- Acute or severe bronchial asthma in an unmonitored setting or in the absence of resuscitative equipment [see WARNINGS]
- Known or suspected gastrointestinal obstruction, including paralytic ileus [see WARNINGS]
- Hypersensitivity to levorphanol or any of the formulation excipients (e.g., anaphylaxis) [see WARNINGS]

WARNINGS

Addiction, Abuse, and Misuse

Levorphanol tartrate tablets contains levorphanol, a Schedule II controlled substance. As an opioid, Levorphanol tartrate tablets exposes users to the risks of addiction, abuse, and misuse [see DRUG ABUSE AND DEPENDENCE].

Although the risk of addiction in any individual is unknown, it can occur in patients appropriately prescribed Levorphanol tartrate tablets. Addiction can occur at recommended dosages and if the drug is misused or abused. The risk of opioid-related overdose or overdose-related death is increased with higher opioid doses, and this risk persists over the course of therapy. In postmarketing studies, addiction, abuse, misuse, and fatal and non-fatal opioid overdose were observed in patients with long-term opioid use [see ADVERSE REACTIONS].

Assess each patient's risk for opioid addiction, abuse, or misuse prior to prescribing levorphanol tartrate tablets, and reassess all patients receiving levorphanol tartrate tablets for the development of these behaviors and conditions. Risks are increased in patients with a personal or family history of substance abuse (including drug or alcohol abuse or addiction) or mental illness (e.g., major depression). The potential for these risks should not, however, prevent the proper management of pain in any given patient. Patients at increased risk may be prescribed opioids such as levorphanol tartrate tablets, but use in such patients necessitates intensive counseling about the risks and proper use of levorphanol tartrate tablets along with frequent reevaluation for signs of addiction, abuse and misuse. Consider recommending or prescribing an opioid overdose reversal agent [see WARNINGS, Life-Threatening Respiratory Depression; DOSAGE AND ADMINISTRATION, Patient Access to Naloxone for the Emergency Treatment of Opioid Overdose].

Opioids are sought for nonmedical use and are subject to diversion from legitimate prescribed use. Consider these risks when prescribing or dispensing levorphanol tartrate tablets. Strategies to reduce these risks include prescribing the drug in smallest appropriate quantity and advising the patient on careful storage of the drug during the course of treatment and proper disposal of unused drug. Contact local state professional licensing board or state-controlled substances authority for information on how to prevent and detect abuse or diversion of this product.

Life Threatening Respiratory Depression

Serious, life-threatening, or fatal respiratory depression has been reported with the use of opioids even when used as recommended. Respiratory depression, if not immediately recognized and treated, may lead to respiratory arrest and death. Management of respiratory depression may include close observation, supportive measures, and use of opioid overdose reversal agents, depending on the patient's clinical status [see OVERDOSAGE]. Carbon dioxide (CO2) retention from opioid-induced respiratory depression can exacerbate the sedating effects of opioids.

While serious, life-threatening, or fatal respiratory depression can occur at any time during the use of levorphanol tartrate tablets, the risk is greatest during the initiation of therapy or following a dosage increase.

To reduce the risk of respiratory depression, proper dosing and titration of levorphanol tartrate tablets are essential [see DOSAGE AND ADMINISTRATION]. Overestimating the levorphanol tartrate tablets dosage when converting patients from another opioid product can result in a fatal overdose with the first dose.

Accidental ingestion of even one dose of levorphanol tartrate tablets, especially by children, can result in respiratory depression and death due to an overdose of levorphanol tartrate tablets.

Educate patients and caregivers on how to recognize respiratory depression and emphasize the importance of calling 911 or getting emergency medical help right away in the event of a known or suspected overdose [see PRECAUTIONS, Information for Patients/Caregivers].

The initial dose of levorphanol tartrate tablets should be reduced by 50% or more when the drug is given to patients with any condition affecting respiratory reserve or in conjunction with other drugs affecting the respiratory center. Subsequent doses should then be individually titrated according to the patient's response.

Opioids can cause sleep-related breathing disorders including central sleep apnea (CSA) and sleep-related hypoxemia. Opioid use increases the risk of CSA in a dose-dependent fashion. In patients who present with CSA, consider decreasing the opioid dosage using best practices for opioid taper [see DOSAGE AND ADMINISTRATION].

Patient Access to an Opioid Overdose Reversal Agent for the Emergency Treatment of Opioid Overdose

Inform patients and caregivers about opioid overdose reversal agents (e.g., naloxone, nalmefene). Discuss the importance of having access to an opioid overdose reversal agent, especially if the patient has risk factors for overdose (e.g., concomitant use of CNS depressants, a history of opioid use disorder, or prior opioid overdose) or if there are household members (including children) or other close contacts at risk for accidental ingestion or opioid overdose. The presence of risk factors for overdose should not prevent the management of pain in any patient [see WARNINGS].
Discuss the options for obtaining an opioid overdose reversal agent (e.g., prescription, over-the-counter, or as part of a community-based program).
There are important differences among the opioid overdose reversal agents, such as route of administration, product strength, approved patient age range, and pharmacokinetics. Be familiar with these differences, as outlined in the approved labeling for those products, prior to recommending or prescribing such an agent.
Educate patients and caregivers on how to recognize respiratory depression, and how to use an opioid overdose reversal agent for the emergency treatment of opioid overdose. Emphasize the importance of calling 911 or getting emergency medical help, even if an opioid overdose reversal agent is administered [see WARNINGS, OVERDOSAGE].

Risks from Concomitant Use with Benzodiazepines or Other CNS Depressants

Profound sedation, respiratory depression, coma, and death may result from the concomitant use of levorphanol tartrate tablets with benzodiazepines and/or other CNS depressants, including alcohol (e.g., non-benzodiazepine sedatives/hypnotics, anxiolytics, tranquilizers, muscle relaxants, general anesthetics, antipsychotics, gabapentinoids [gabapentin or pregabalin], and other opioids). Because of these risks, reserve concomitant prescribing of these drugs for use in patients for whom alternative treatment options are inadequate.

Observational studies have demonstrated that concomitant use of opioid analgesics and benzodiazepines increases the risk of drug-related mortality compared to use of opioid analgesics alone. Because of similar pharmacological properties, it is reasonable to expect similar risk with the concomitant use of other CNS depressant drugs with opioid analgesics [see PRECAUTIONS, Drug Interactions].

If the decision is made to prescribe a benzodiazepine or other CNS depressant concomitantly with an opioid analgesic, prescribe the lowest effective dosages and minimum durations of concomitant use. In patients already receiving an opioid analgesic, prescribe a lower initial dose of the benzodiazepine or other CNS depressant than indicated in the absence of an opioid, and titrate based on clinical response. If an opioid analgesic is initiated in a patient already taking a benzodiazepine or other CNS depressant, prescribe a lower initial dose of the opioid analgesic, and titrate based on clinical response. Inform patients and caregivers of this potential interaction, educate them on the signs and symptoms of respiratory depression (including sedation).

If concomitant use is warranted, consider recommending or prescribing an opioid overdose reversal agent [see WARNINGS, Life-Threatening Respiratory Depression; DOSAGE AND ADMINISTRATION, Patient Access to Naloxone for the Emergency Treatment of Opioid Overdose and OVERDOSAGE].

Advise both patients and caregivers about the risks of respiratory depression and sedation when levorphanol tartrate tablets are used with benzodiazepines or other CNS depressants (including alcohol and illicit drugs). Advise patients not to drive or operate heavy machinery until the effects of concomitant use of the benzodiazepine or other CNS depressant have been determined. Screen patients for risk of substance use disorders, including opioid abuse and misuse, and warn them of the risk for overdose and death associated with the use of additional CNS depressants including alcohol and illicit drugs [see PRECAUTIONS; Information for Patients/Caregivers, Drug Interactions].

Neonatal Opioid Withdrawal Syndrome

Use of levorphanol tartrate tablets for an extended period of time during pregnancy can result in withdrawal in the neonate. Neonatal opioid withdrawal syndrome, unlike opioid withdrawal syndrome in adults, may be life-threatening if not recognized and treated, and requires management according to protocols developed by neonatology experts. Observe newborns for signs of neonatal opioid withdrawal syndrome and manage accordingly. Advise pregnant women using opioids for an extended period of time of the risk of neonatal opioid withdrawal syndrome and ensure that appropriate treatment will be available [see PRECAUTIONS; Information for Patients/Caregivers, Pregnancy].

Opioid Analgesic Risk Evaluation and Mitigation Strategy (REMS)

To ensure that the benefits of opioid analgesics outweigh the risks of addiction, abuse, and misuse, the Food and Drug Administration (FDA) has required a Risk Evaluation and Mitigation Strategy (REMS) for these products. Under the requirements of the REMS, drug companies with approved opioid analgesic products must make REMS-compliant education programs available to healthcare providers. Healthcare providers are strongly encouraged to do all of the following:

- Complete a REMS-compliant education program offered by an accredited provider of continuing education (CE) or another education program that includes all the elements of the FDA Education Blueprint for Health Care Providers Involved in the Management or Support of Patients with Pain.
- Discuss the safe use, serious risks, and proper storage and disposal of opioid analgesics with patients and/or their caregivers every time these medicines are prescribed. The Patient Counseling Guide (PCG) can be obtained at this link: www.fda.gov/OpioidAnalgesicREMSPCG.
- Emphasize to patients and their caregivers the importance of reading the Medication Guide that they will receive from their pharmacist every time an opioid analgesic is dispensed to them.
- Consider using other tools to improve patient, household, and community safety, such as patient- prescriber agreements that reinforce patient-prescriber responsibilities.

To obtain further information on the opioid analgesic REMS and for a list of accredited REMS CME/CE, call 800-503-0784, or log on to www.opioidanalgesicrems.com.The FDA Blueprint can be found at www.fda.gov/OpioidAnalgesicREMSBlueprint.

Opioid-Induced Hyperalgesia and Allodynia

Opioid-Induced Hyperalgesia (OIH) occurs when an opioid analgesic paradoxically causes an increase in pain, or an increase in sensitivity to pain. This condition differs from tolerance, which is the need for increasing doses of opioids to maintain a defined effect [see DEPENDENCE]. Symptoms of OIH include (but may not be limited to) increased levels of pain upon opioid dosage increase, decreased levels of pain upon opioid dosage decrease, or pain from ordinarily non-painful stimuli (allodynia). These symptoms may suggest OIH only if there is no evidence of underlying disease progression, opioid tolerance, opioid withdrawal, or addictive behavior.

Cases of OIH have been reported, both with short-term and longer-term use of opioid analgesics. Though the mechanism of OIH is not fully understood, multiple biochemical pathways have been implicated. Medical literature suggests a strong biologic plausibility between opioid analgesics and OIH and allodynia. If a patient is suspected to be experiencing OIH, carefully consider appropriately decreasing the dose of the current opioid analgesic, or opioid rotation (safely switching the patient to a different opioid moiety) [see DOSAGE AND ADMINISTRATION, WARNINGS].

Life-Threatening Respiratory Depression in Patients with Chronic Pulmonary Disease or in Elderly, Cachectic, or Debilitated Patient

The use of levorphanol tartrate tablets in patients with acute or severe bronchial asthma in an unmonitored setting or in the absence of resuscitative equipment is contraindicated.

Patients with Chronic Pulmonary Disease:Patients treated with levorphanol tartrate tablets with significant chronic obstructive pulmonary disease or cor pulmonale, and those with a substantially decreased respiratory reserve, hypoxia, hypercapnia, or pre-existing respiratory depression are at increased risk of decreased respiratory drive including apnea, even at recommended dosages of levorphanol [see WARNINGS].

Elderly, Cachectic, or Debilitated Patients:Life-threatening respiratory depression is more likely to occur in elderly, cachectic, or debilitated patients because they may have altered pharmacokinetics or altered clearance compared to younger, healthier patients [see WARNINGS].

Regularly evaluate patients, particularly when initiating and titrating levorphanol tartrate tablets and when levorphanol tartrate tablets are given concomitantly with other drugs that depress respiration [see WARNINGS]. Alternatively, consider the use of non-opioid analgesics in these patients.

Adrenal Insufficiency

Cases of adrenal insufficiency have been reported with opioid use, more often following greater than 1 month of use. Presentation of adrenal insufficiency may include non-specific symptoms and signs including nausea, vomiting, anorexia, fatigue, weakness, dizziness, and low blood pressure. If adrenal insufficiency is suspected, confirm the diagnosis with diagnostic testing as soon as possible. If adrenal insufficiency is diagnosed, treat with physiologic replacement doses of corticosteroids. Wean the patient off of the opioid to allow adrenal function to recover and continue corticosteroid treatment until adrenal function recovers. Other opioids may be tried as some cases reported use of a different opioid without recurrence of adrenal insufficiency. The information available does not identify any particular opioids as being more likely to be associated with adrenal insufficiency.

Cardiovascular Effects

The use of levorphanol tartrate tablets in acute myocardial infarction or in cardiac patients with myocardial dysfunction or coronary insufficiency should be limited because the effects of levorphanol tartrate tablets on the work of the heart are unknown.

Severe Hypotension

Levorphanol tartrate tablets may cause severe hypotension including orthostatic hypotension and syncope in ambulatory patients. There is increased risk in patients whose ability to maintain blood pressure has already been compromised by a reduced blood volume or concurrent administration of certain CNS depressant drugs (e.g., phenothiazines or general anesthetics) [see PRECAUTIONS; Drug Interactions]. Regularly evaluate these patients for signs of hypotension after initiating or titrating the dosage of levorphanol tartrate tablets. In patients with circulatory shock levorphanol tartrate tablets may cause vasodilatation that can further reduce cardiac output and blood pressure. Avoid the use of levorphanol tartrate tablets with circulatory shock.

Risks of Use in Patients with Increased Intracranial Pressure, Brain Tumors, Head Injury, or Impaired Consciousness

In patients who may be susceptible to the intracranial effects of CO2 retention (e.g., those with evidence of increased intracranial pressure or brain tumors), levorphanol tartrate tablets may reduce respiratory drive, and the resultant CO2 retention can further increase intracranial pressure. Monitor such patients for signs of sedation and respiratory depression, particularly when initiating therapy with levorphanol tartrate tablets.

Opioids may also obscure the clinical course in a patient with a head injury. Avoid the use of levorphanol tartrate tablets in patients with impaired consciousness or coma.

Risks of Gastrointestinal Complications

Levorphanol tartrate tablets are contraindicated in patients with known or suspected gastrointestinal obstruction, including paralytic ileus.

The levorphanol in levorphanol tartrate tablets may cause spasm of the sphincter of Oddi. Levorphanol tartrate tablets has been shown to cause moderate to marked rises in pressure in the common bile duct when given in analgesic doses. It is not recommended for use in biliary surgery.

Opioids may cause increases in serum amylase. Regularly evaluate patients with biliary tract disease, including acute pancreatitis, for worsening symptoms.

Cases of opioid-induced esophageal dysfunction (OIED) have been reported in patients taking opioids. The risk of OIED may increase as the dose and/or duration of opioids increases. Regularly evaluate patients for signs and symptoms of OIED (e.g., dysphagia, regurgitation, non-cardiac chest pain), and if necessary, adjust opioid therapy as clinically appropriate [see CLINICAL PHARMACOLOGY].

Increased Risk of Seizures in Patients with Seizure Disorders

The levorphanol in levorphanol tartrate tablets may increase the frequency of seizures in patients with seizure disorders, and may increase the risk of seizures occurring in other clinical settings associated with seizures. Regularly evaluate patients with a history of seizure disorders for worsened seizure control during levorphanol tartrate tablets therapy.

Withdrawal

Do not rapidly reduce or abruptly discontinue levorphanol in a patient physically dependent on opioids. When discontinuing levorphanol in a physically dependent patient, gradually taper the dosage. Rapid tapering of levorphanol in a patient physically dependent on opioids may lead to a withdrawal syndrome and return of pain [see DOSAGE AND ADMINISTRATION, DRUG ABUSE AND DEPENDENCE].

Additionally, avoid the use of mixed agonist/antagonist (e.g., pentazocine, nalbuphine, and butorphanol) or partial agonist (e.g., buprenorphine) analgesics in patients who are receiving a full opioid agonist analgesic, including levorphanol. In these patients, mixed agonist/antagonist and partial agonist analgesics may reduce the analgesic effect and/or precipitate withdrawal symptoms [see Drug Interactions].

Risks of Driving and Operating Machinery

Levorphanol tartrate tablets may impair the mental or physical abilities needed to perform potentially hazardous activities such as driving a car or operating machinery. Warn patients not to drive or operate dangerous machinery unless they are tolerant to the effects of levorphanol tartrate tablets and know how they will react to the medication [see PRECAUTIONS; Information for Patients/Caregivers].

Use in Liver Disease

Levorphanol tartrate tablets should be administered with caution to patients with extensive liver disease who may be vulnerable to excessive sedation due to increased pharmacodynamic sensitivity or impaired metabolism of the drug

PRECAUTIONS

Information for Patients/Caregivers

Storage and Disposal

Because of the risks associated with accidental ingestion, misuse, and abuse, advise patients to store levorphanol tartrate tablets securely, out of sight and reach of children, and in a location not accessible by others, including visitors to the home .Inform patients that leaving levorphanol tartrate tablets unsecured can pose a deadly risk to others in the home [see WARNINGS, DRUG ABUSE AND DEPENDENCE].

Advise patients and caregivers that when medicines are no longer needed, they should be disposed of promptly. Expired, unwanted, or unused levorphanol tartrate tablets should be disposed of by flushing the unused medication down the toilet if a drug take-back option is not readily available. Inform patients that they can visit www.fda.gov/drugdisposalfor a complete list of medicines recommended for disposal by flushing, as well as additional information on disposal of unused medicines.

Advise the patient to read the FDA-approved patient labeling (Medication Guide).

Addiction, Abuse, and Misuse

Inform patients that the use of levorphanol tartrate tablets even when taken as recommended, can result in addiction, abuse, and misuse, which can lead to overdose and death [see WARNINGS]. Instruct patients not to share levorphanol tartrate tablets with others and to take steps to protect levorphanol tartrate tablets from theft or misuse.

Life-Threatening Respiratory Depression

Inform patients of the risk of life-threatening respiratory depression, including information that the risk is greatest when starting levorphanol tartrate tablets or when the dosage is increased, and that it can occur even at recommended dosages.

Educate patients and caregivers on how to recognize respiratory depression and emphasize the importance of calling 911 or getting emergency medical help right away in the event of a known or suspected overdose [see WARNINGS, Life Threatening Respiratory Depression].

Accidental Ingestion

Inform patients that accidental ingestion, especially by children, may result in respiratory depression or death [see WARNINGS].

Interactions with Benzodiazepine and Other CNS Depressants

Inform patients and caregivers that potentially fatal additive effects may occur if levorphanol tartrate tablets are used with benzodiazepine or other CNS depressants, including alcohol (e.g., non-benzodiazepine sedative/hypnotics, anxiolytics, tranquilizers, muscle relaxants, general anesthetics, antipsychotics, gabapentinoids [gabapentin or pregabalin], and other opioids), and not to use these drugs concomitantly unless supervised by a healthcare provider [see WARNINGS, PRECAUTIONS; Drug Interactions].

Patient Access to Opioid Overdose Reversal Agentfor the Emergency Treatment of Opioid Overdose

Inform patients and caregivers about opioid overdose reversal agents (e.g., naloxone, nalmefene). Discuss the importance of having access to an opioid overdose reversal agent, especially if the patient has risk factors for overdose (e.g., concomitant use of CNS depressants, a history of opioid use disorder, or prior opioid overdose) or if there are household members (including children) or other close contacts at risk for accidental ingestion or opioid overdose.
Discuss with the patient the options for obtaining an opioid overdose reversal agent (e.g., prescription, over-thecounter,
or as part of a community-based program) [see WARNINGS, DOSAGE AND ADMINISTRATION].

Educate patients and caregivers on how to recognize the signs and symptoms of an overdose.

Explain to patients and caregivers that effects of opioid overdose reversal agents like naloxone and nalmefene are temporary, and that they must call 911 or get emergency medical help right away in all cases of known or suspected opioid overdose, even if an opioid overdose reversal agent is administered [see OVERDOSAGE].

Advise patients and caregivers:

- how to treat with overdose reversal agent in the event of an opioid overdose
- to tell family and friends about the opioid overdose reversal agent, and to keep in in a place where family and friends can access it in an emergency
- To read the Patient Information (or other educational material) that will come with their opioid overdose reversal agent. Emphasize the importance of doing this before an opioid emergency happens, so the patient and caregiver will know what to do

Hyperalgesia and Allodynia

Inform patients and caregivers not to increase opioid dosage without first consulting a clinician. Advise patients to seek medical attention if they experience symptoms of hyperalgesia, including worsening pain, increased sensitivity to pain, or new pain [see WARNINGS; ADVERSE REACTIONS].

Serotonin Syndrome

Inform patients that opioids could cause a rare but potentially life-threatening condition resulting from concomitant administration of serotonergic drugs. Warn patients of the symptoms of serotonin syndrome and to seek medical attention right away if symptoms develop.

Instruct patients to inform their physician or healthcare provider if they are taking, or plan to take serotonergic medications [see PRECAUTIONS; Drug Interactions].

Important Discontinuation Instructions

In order to avoid developing withdrawal symptoms, instruct patients not to discontinue levorphanol tartrate tablets without first discussing a tapering plan with the prescriber [see DOSAGE AND ADMINISTRATION].

Driving or Operating Heavy Machinery

Inform patients that levorphanol tartrate tablets may impair the ability to perform potentially hazardous activities such as driving a car or operating heavy machinery. Advise patients not to perform such tasks until they know how they will react to the medication [see PRECAUTIONS].

Constipation

Advise patients of the potential for severe constipation, including management instructions and when to seek medical attention [see ADVERSE REACTIONS].

Adrenal Insufficiency

Inform patients that opioids could cause adrenal insufficiency, a potentially life-threatening condition. Adrenal insufficiency may present with non-specific symptoms and signs such as nausea, vomiting, anorexia, fatigue, weakness, dizziness, and low blood pressure. Advise patients to seek medical attention if they experience a constellation of these symptoms [see WARNINGS].

Hypotension

Inform patients that levorphanol tartrate tablets may cause orthostatic hypotension and syncope. Instruct patients how to recognize symptoms of low blood pressure and how to reduce the risk of serious consequences should hypotension occur (e.g., sit or lie down, carefully rise from a sitting or lying position) [see WARNINGS].

Anaphylaxis

Inform patients that anaphylaxis has been reported with ingredients contained in levorphanol tartrate tablets. Advise patients how to recognize such a reaction, and if they develop signs of allergy such as a rash or difficulty breathing to stop taking levorphanol tartrate tablets and seek medical attention. [see CONTRAINDICATIONS, ADVERSE REACTIONS].

Pregnancy

Neonatal Opioid Withdrawal Syndrome

Inform female patients of reproductive potential that use of levorphanol tartrate tablets for an extended period of time during pregnancy can result in neonatal opioid withdrawal syndrome, which may be life-threatening if not recognized and treated [see WARNINGS, PRECAUTIONS; Pregnancy]

Embryo-Fetal Toxicity

Inform female patients of reproductive potential that levorphanol tartrate tablets can cause fetal harm and to inform the prescriber of a known or suspected pregnancy [see WARNINGS, PRECAUTIONS; Pregnancy].

Lactation

Advise nursing mothers to carefully observe infants for increased sleepiness (more than usual), breathing difficulties, or limpness. Instruct nursing mothers to see immediate medical care if they notice these signs [see PRECAUTIONS; Nursing Mothers].

Infertility

Inform patients that use of opioids for an extended period of time may cause reduced fertility. It is not known whether these effects on fertility are reversible [see ADVERSE REACTIONS].

Disposal of Unused Levorphanol

Advise patients to flush unused levorphanol tartrate tablets down the toilet.

Drug Interactions

Benzodiazepines and Other Central Nervous System (CNS) Depressants

Due to additive pharmacologic effect, the concomitant use of benzodiazepines and other CNS depressants, such as benzodiazepines, and other sedative hypnotics, anxiolytics, and tranquilizers, muscle relaxants, general anesthetics, antipsychotics, gabapentinoids (gabapentin or pregabalin), and other opioids, including alcohol, can increase the risk of hypotension, respiratory depression, profound sedation, coma, and death.

Reserve concomitant prescribing of these drugs for use in patients for whom alternative treatment options are inadequate. Limit dosages and durations to the minimum required. Inform patients and caregivers of this potential interaction, educate them on the signs and symptoms of respiratory depression (including sedation). If concomitant use is warranted, consider recommending or prescribing an opioid overdose reversal agent [see WARNINGS, DOSAGE AND ADMINISTRATION ].

Serotonergic Drugs

The concomitant use of opioids with other drugs that affect the serotonergic neurotransmitter system, such as selective serotonin reuptake inhibitors (SSRIs), serotonin and norepinephrine reuptake inhibitors (SNRIs), tricyclic antidepressants (TCAs), triptans, 5-HT3 receptor antagonists, drugs that affect the serotonin neurotransmitter system (e.g., mirtazapine, trazodone, tramadol), certain muscle relaxants (i.e., cyclobenzaprine, metaxalone), and monoamine oxidase (MAO) inhibitors (those intended to treat psychiatric disorders and also others, such as linezolid and intravenous methylene blue), has resulted in serotonin syndrome. [see PRECAUTIONS; Information for Patients/Caregivers].

If concomitant use is warranted, frequently evaluate the patient, particularly during treatment initiation and dose adjustment. Discontinue levorphanol tartrate tablets if serotonin syndrome is suspected.

Mixed Agonist/Antagonist and Partial Opioid Analgesics

The concomitant use of opioid with other opioid analgesics, such as butorphanol, nalbuphine, pentazocine, may reduce the analgesic effect of levorphanol tartrate tablets and precipitate withdrawal symptoms.

Advise patient to avoid concomitant use of these drugs.

Muscle Relaxants (examples: cyclobenzaprine, metaxalone)

Levorphanol may enhance the neuromuscular blocking action of skeletal muscle relaxants and produce an increased degree of respiratory depression.

If concomitant use is warranted, because respiratory depression may be greater than otherwise expected, decrease the dosage of levorphanol tartrate tablets and/or the muscle relaxant as necessary. Due to the risk of respiratory depression with the concomitant use of skeletal muscle relaxants and opioids, consider recommending or prescribing an opioid overdose reversal agent [see WARNINGS, DOSAGE AND ADMINISTRATION].

Diuretics

Opioids can reduce the efficacy of diuretics by inducing the release of antidiuretic hormone.

If concomitant use is warranted, evaluate patients for signs of diminished diuresis and/or effects on blood pressure and increase the dosage of the diuretic as needed.

Anticholinergic Drugs

The concomitant use of anticholinergic drugs may increase risk of urinary retention and/or severe constipation, which may lead to paralytic ileus.

If concomitant use is warranted, evaluate patients for signs of urinary retention or reduced gastric motility when levorphanol tartrate tablets are used concomitantly with anticholinergic drugs.

Carcinogenesis, Mutagenesis, Impairment of Fertility

Carcinogenesis

Long-term studies in animals to evaluate the carcinogenic potential of levorphanol have not been conducted.

Mutagenesis

Animal studies to evaluate the mutagenic potential of levorphanol have not been conducted.

Impairment of Fertility

Animal studies to determine the effect of levorphanol on fertility have not been conducted.

Infertility

Use of opioids for an extended period of time may cause reduced fertility in females and males of reproductive potential. It is not known whether these effects on fertility are reversible [see ADVERSE REACTIONS].

Pregnancy

Risk Summary

Use of opioid analgesics for an extended period of time during pregnancy may cause neonatal opioid withdrawal syndrome [see WARNINGS]. Available data with levorphanol tartrate tablets in pregnant women are insufficient to inform a drug-associated risk for major birth defects and miscarriage.

In animal reproduction studies, oral levorphanol produced malformations and nearly 50% embryo lethality in mice at 10 and 12 times the human daily dose of 12 mg/day, respectively. Paternal exposure to levorphanol prior to mating to an untreated female resulted in reduced litter birth weights, developmental delays, and aberrant behavior in a swim maze at 34 times the human daily dose of 12 mg/day.

All pregnancies have a background risk of birth defect, loss, or other adverse outcomes. In the U.S. general population, the estimated background risk of major birth defects and miscarriage in clinically recognized pregnancies is 2-4% and 15-20%, respectively.

Clinical Considerations

Fetal/Neonatal Adverse Reactions

Use of opioid analgesics for an extended period of time during pregnancy for medical or nonmedical purposes can result in physical dependence in the neonate and neonatal opioid withdrawal syndrome shortly after birth.

Neonatal opioid withdrawal syndrome presents as irritability, hyperactivity and abnormal sleep pattern, high pitched cry, tremor, vomiting, diarrhea, and failure to gain weight. The onset, duration, and severity of neonatal opioid withdrawal syndrome vary based on the specific opioid used, duration of use, timing and amount of last maternal use, and rate of elimination of the drug by the newborn. Observe newborns for symptoms of neonatal opioid withdrawal syndrome and manage accordingly [see WARNINGS].

Labor or Delivery

Opioids cross the placenta and may produce respiratory depression and psycho-physiologic effects in neonates. An opioid overdose reversal agent, such as naloxone or nalmefene, must be available for reversal of opioid-induced respiratory depression in the neonate. Levorphanol tartrate tablets are not recommended for use in pregnant women during or immediately prior to labor, when other analgesic techniques are more appropriate. Opioid analgesics, including levorphanol tartrate tablets can prolong labor through actions which temporarily reduce the strength, duration, and frequency of uterine contractions.

However, this effect is not consistent and may be offset by an increased rate of cervical dilation, which tends to shorten labor.

Monitor neonates exposed to opioid analgesics during labor for signs of excess sedation and respiratory depression.

Animal Data

In a published study, levorphanol has been shown to cause central nervous system malformations consistent with neural tube defects (kinking of the spinal cord, hydromyelia, dilation of the fourth ventricle, and brachyury) in pregnant mice when given a single subcutaneous dose of 25 mg/kg (10 times the human daily dose of 12 mg/day based on a body surface area comparison) on Gestation Day 9.

Subcutaneous administration of 30 mg/kg levorphanol to pregnant mice on Gestation Day 9 resulted in approximately 50% mortality of the mouse embryos (12 times the human daily dose of 12 mg/day).

In another published study, male mice were injected subcutaneously twice daily with increasing daily doses of levorphanol up to 42 mg/kg/day (34 times the human daily dose of 12 mg based on body surface area) for 5.5 to 8.5 days prior to mating with an untreated female. Paternal exposure to levorphanol resulted in reduced birth weights of the litters, developmental delays in the offspring, and aberrant swim patterns in the progeny when measured at 6.5 to 8.5 weeks of age.

Lactation

Risk Summary

The developmental and health benefits of breastfeeding should be considered along with the mother's clinical need for levorphanol tartrate tablets and any potential adverse effects on the breastfed infant from levorphanol tartrate tablets or from the underlying maternal condition.

Clinical Considerations

Infants exposed to levorphanol tartrate tablets through breast milk should be monitored for excess sedation and respiratory depression. Withdrawal symptoms can occur in breastfed infants when maternal administration of an opioid analgesic is stopped, or when breast-feeding is stopped.

Data

Studies of levorphanol concentrations in breast milk have not been performed. However, morphine, which is structurally similar to levorphanol, is excreted in human milk. Because of the potential for serious adverse reactions from levorphanol in nursing infants, a decision should be made whether to discontinue nursing or to discontinue the drug, taking into account the importance of the drug to the mother.

Pediatric Use

Levorphanol tartrate tablets are not recommended in children under the age of 18 years as the safety and efficacy of the drug in this population has not been established.

Geriatric Use

Elderly patients (aged 65 years or older) may have increased sensitivity to levorphanol. In general, use caution when selecting a dosage for an elderly patient, usually starting at the low end of the dosing range, reflecting the greater frequency of decreased hepatic, renal, or cardiac function and of concomitant disease or other drug therapy. The initial dose of levorphanol tartrate tablets should be reduced by 50% or more in the infirm elderly patient.

Respiratory depression is the chief risk for elderly patients treated with opioids, and has occurred after large initial doses were administered to patients who were not opioid- tolerant or when opioids were co-administered with other agents that depress respiration. Titrate the dosage of levorphanol tartrate tablets slowly in geriatric patients and frequently reevaluate the patient for signs of central nervous system and respiratory depression [see WARNINGS].

This drug is known to be substantially excreted by the kidney, and the risk of adverse reactions to this drug may be greater in patients with impaired renal function. Because elderly patients are more likely to have decreased renal function, care should be taken in dose selection, and it may be useful to regularly evaluate renal function.

ADVERSE REACTIONS

In approximately 1400 patients treated with levorphanol tartrate tablets in controlled clinical trials, the type and incidence of side effects were those expected of an opioid analgesic, and no unforeseen or unusual toxicity was reported.

Drugs of this type are expected to produce a cluster of typical opioid effects in addition to analgesia, consisting of nausea, vomiting, altered mood and mentation, pruritus, flushing, difficulties in urination, constipation, and biliary spasm. The frequency and intensity of these effects appears to be dose related. Although listed as adverse events these are expected pharmacologic actions of these drugs and should be interpreted as such by the clinician.

The following adverse events have been reported with the use of levorphanol tartrate tablets:

Body as a Whole:abdominal pain, dry mouth, sweating

Cardiovascular System:cardiac arrest, shock, hypotension, arrhythmias including bradycardia and tachycardia, palpitations, extra-systoles

Digestive System:nausea, vomiting, dyspepsia, biliary tract spasm

Nervous System:coma, suicide attempt, convulsions, depression, dizziness, confusion, lethargy, abnormal dreams, abnormal thinking, nervousness, drug withdrawal, hypokinesia, dyskinesia, hyperkinesia, CNS stimulation, personality disorder, amnesia, insomnia

Respiratory System:apnea, cyanosis, hypoventilation

Skin & Appendages:pruritus, urticaria, rash, injection site reaction

Special Senses:abnormal vision, pupillary disorder, diplopia

Urogenital System:kidney failure, urinary retention, difficulty urinating

Postmarketing Experience

The following adverse reactions have been identified during post approval use of levorphanol. Because these reactions are reported voluntarily from a population of uncertain size, it is not always possible to reliably estimate their frequency or establish a causal relationship to drug exposure.

- Serotonin syndrome: Cases of serotonin syndrome, a potentially life-threatening condition, have been reported during concomitant use of opioids with serotonergic drugs.
- Adrenal insufficiency: Cases of adrenal insufficiency have been reported with opioid use, more often following greater than one month of use.
- Anaphylaxis: Anaphylaxis has been reported with ingredients contained in levorphanol tartrate tablets.
- Androgen deficiency: Cases of androgen deficiency have occurred with use of opioids for an extended period of time [see CLINICAL PHARMACOLOGY].
- Hyperalgesia and Allodynia:Cases of hyperalgesia and allodynia have been reported with opioid therapy of any duration [see WARNINGS].
- Hypoglycemia: Cases of hypoglycemia have been reported in patients taking opioids. Most reports were in patients with at least one predisposing risk factor (e.g., diabetes).

Opioid-induced esophageal dysfunction (OIED): Cases of OIED have been reported in patients taking opioids, and may occur more frequently in patients taking higher doses of opioid, and/or in patients taking opioids longer term [see WARNINGS].

Adverse Reactions from Observational Studies

A prospective, observational cohort study estimated the risks of addiction, abuse, and misuse in patients initiating long-term use of Schedule II opioid analgesics between 2017 and 2021. Study participants included in one or more analyses had been enrolled in selected insurance plans or health systems for at least one year, were free of at least one outcome at baseline, completed a minimum number of follow-up assessments, and either: 1) filled multiple extended-release/long-acting opioid analgesic prescriptions during a 90 day period (n=978); or 2) filled any Schedule II opioid analgesic prescriptions covering at least 70 of 90 days (n=1,244). Those included also had no dispensing of the qualifying opioids in the previous 6 months.

Over 12 months:

- approximately 1% to 6% of participants across the two cohorts newly met criteria for addiction, as assessed with two validated intervie wbased measures of moderate-to-severe opioid use disorder based on Diagnostic and Statistical Manual of Mental Disorders, Fifth Edition (DSM-5) criteria, and
- approximately 9% and 22% of participants across the two cohorts newly met criteria for prescription opioid abuse and misuse [defined in DRUG ABUSE AND DEPENDENCE], respectively, as measured with a validated self-reported instrument.

A retrospective, observational cohort study estimated the risk of opioid involved overdose or opioid overdoserelated death in patients with new long-term use of Schedule II opioid analgesics from 2006 through 2016 (n=220,249). Included patients had been enrolled in either one of two commercial insurance programs, one managed care program, or one Medicaid program for at least 9 months. New long-term use was defined as having Schedule II opioid analgesic prescriptions covering at least 70 days’ supply over the 3 months prior to study entry and none during the preceding 6 months. Patients were excluded if they had an opioid-involved overdose in the 9 months prior to study entry. Overdose was measured using a validated medical code-based algorithm with linkage
to the National Death Index database. The 5-year cumulative incidence estimates for opioid-involved overdose or opioid overdose-related death ranged from approximately 1.5% to 4% across study sites, counting only the first event during follow-up. Approximately 17% of first opioid overdoses observed over the entire study period (5 to 11 years, depending on the study site) were fatal. Higher baseline opioid dose was the strongest and most consistent predictor of opioid-involved overdose or opioid overdose-related death. Study exclusion criteria may have selected patients at lower risk of overdose, and substantial loss to follow-up (approximately 80%) also may have biased estimates.
The risk estimates from the studies described above may not be generalizable to all patients receiving opioid analgesics, such as those with exposures shorter or longer than the duration evaluated in the studies.

DRUG ABUSE AND DEPENDENCE

Controlled Substance

Levorphanol tartrate tablets contains levorphanol, a Schedule II controlled substance.

Abuse

Levorphanol tartrate tablets contain levorphanol, a substance with high potential for misuse and abuse, which can lead to the development of substance use disorder, including addiction [see WARNINGS].

Misuse is the intentional use, for therapeutic purposes, of a drug by an individual in a way other than prescribed by a healthcare provider or for whom it was not prescribed.

Abuse is the intentional, non-therapeutic use of a drug, even once, for its desirable psychological or physiological effects.

Drug addiction is a cluster of behavioral, cognitive, and physiological phenomena that may include a strong desire to take the drug, difficulties in controlling drug use (e.g., continuing drug use despite harmful consequences, giving a higher priority to drug use than other activities and obligations), and possible tolerance or physical dependence.

Misuse and abuse of levorphanol tartrate tablets increases risk of overdose, which may lead to central nervous system and respiratory depression, hypotension, seizures, and death. The risk is increased with concurrent abuse of levorphanol tartrate tablets with alcohol and other CNS depressants. Abuse of and addiction to opioids in some individuals may not be accompanied by concurrent tolerance and symptoms of physical dependence. In addition, abuse of opioids can occur in the absence of addiction.

All patients treated with opioids require careful and frequent reevaluation for signs of misuse, abuse, and addiction, because use of opioid analgesic products carries the risk of addiction even under appropriate medical use. Patients at high risk of levorphanol tartrate tablets abuse include those with a history of prolonged use of any opioid, including products containing levorphanol, those with a history of drug or alcohol abuse, or those who use levorphanol tartrate tablets in combination with other abused drugs.

“Drug-seeking” behavior is very common in persons with substance use disorders. Drug-seeking tactics include emergency calls or visits near the end of office hours, refusal to undergo appropriate examination, testing, or referral, repeated “loss” of prescriptions, tampering with prescriptions, and reluctance to provide prior medical records or contact information for other treating healthcare provider(s). “Doctor shopping” (visiting multiple prescribers to obtain additional prescriptions) is common among people who abuse drugs and people with substance use disorder. Preoccupation with achieving adequate pain relief can be appropriate behavior in a patient with inadequate pain control.

Levorphanol tartrate tablets, like other opioids, can be diverted for nonmedical use into illicit channels of distribution. Careful record-keeping of prescribing information, including quantity, frequency, and renewal requests, as required by state and federal law, is strongly advised.

Proper assessment of the patient, proper prescribing practices, periodic reevaluation of therapy, and proper dispensing and storage are appropriate measures that help to limit abuse of opioid drugs.

Risks Specific to Abuse of Levorphanol Tartrate Tablets

Abuse of levorphanol tartrate tablets poses a risk of overdose and death. The risk is increased with concurrent use of levorphanol tartrate tablets with alcohol and/or other CNS depressants.

Parenteral drug abuse is commonly associated with transmission of infectious diseases such as hepatitis and HIV.

Dependence

Both tolerance and physical dependence can develop during use of opioid therapy.

Tolerance is a physiological state characterized by a reduced response to a drug after repeated administration (i.e., a higher dose of a drug is required to produce the same effect that was once obtained at a lower dose).

Physical dependence is a state that develops as a result of a physiological adaptation in response to repeated drug use, manifested by withdrawal signs and symptoms after abrupt discontinuation or a significant dose reduction of a drug.

Withdrawal may be precipitated through the administration of drugs with opioid antagonist activity (e.g., naloxone, nalmefene), mixed agonist/antagonist analgesics (e.g., pentazocine, butorphanol, nalbuphine), or partial agonists (e.g., buprenorphine). Physical dependence may not occur to a clinically significant degree until after several days to weeks of continued use.

Do not rapidly reduce or abruptly discontinue levorphanol tartrate tablets in a patient physically dependent on opioids. Rapid tapering of levorphanol tartrate tablets in a patient physically dependent on opioids may lead to serious withdrawal symptoms, uncontrolled pain, and suicide. Rapid discontinuation has also been associated with attempts to find other sources of opioid analgesics, which may be confused with drug-seeking for abuse.

When discontinuing levorphanol tartrate tablets, gradually taper the dosage using a patient-specific plan that considers the following: the dose of levorphanol tartrate tablets the patient has been taking, the duration of treatment, and the physical and psychological attributes of the patient. To improve the likelihood of a successful taper and minimize withdrawal symptoms, it is important that the opioid tapering schedule is agreed upon by the patient. In patients taking opioids for an extended period of time at high doses, ensure that a multimodal approach to pain management, including mental health support (if needed), is in place prior to initiating an opioid analgesic taper [see DOSAGE AND ADMINISTRATION, and WARNINGS].

Infants born to mothers physically dependent on opioids will also be physically dependent and may exhibit respiratory difficulties and withdrawal signs [see PREGNANCY].

OVERDOSAGE

Clinical Presentation

Acute overdose with levorphanol tartrate tablets can be manifested by respiratory depression, somnolence progressing to stupor or coma, skeletal muscle flaccidity, cold and clammy skin, constricted pupils, and, in some cases, pulmonary edema, bradycardia, hypotension, hypoglycemia, partial or complete airway obstruction, atypical snoring, and death. Marked mydriasis rather than miosis may be seen with hypoxia in overdose situations [see CLINICAL PHARMACOLOGY]. Toxic leukoencephalopathy has been reported after opioid overdose and can present hours, days, or weeks after apparent recovery from the initial intoxication.

Treatment of Overdose

In case of overdose, priorities are the reestablishment of a patent and protected airway and institution of assisted or controlled ventilation, if needed. Employ other supportive measures (including oxygen and vasopressors) in the management of circulatory shock and pulmonary edema as indicated. Cardiac arrest or arrhythmias will require advanced life-support measures.

For clinically significant respiratory or circulatory depression secondary to opioid overdose, administer an opioid overdose reversal agent such as naloxone or nalmefene.

Because the duration of opioid reversal is expected to be less than the duration of action of levorphanol in levorphanol tartrate tablets, carefully monitor the patient until spontaneous respiration is reliably reestablished. If the response to an opioid overdose reversal agent is suboptimal or only brief in nature, administer additional reversal agent as directed by the product's prescribing information.

In an individual physically dependent on opioids, administration of the recommended usual dosage of the opioid overdose reversal agent will precipitate an acute withdrawal syndrome. The severity of the withdrawal symptoms experienced will depend on the degree of physical dependence and the dose of the reversal agent administered. If a decision is made to treat serious respiratory depression in the physically dependent patient, administration of the reversal agent should be initiated with care and by titration with smaller than usual doses of the reversal agent.

DOSAGE AND ADMINISTRATION

Important Dosage and Administration Instructions

Levorphanol tartrate tablets should be prescribed only by healthcare professionals who are knowledgeable about the use of opioids and how to mitigate the associated risks.

Use the lowest effective dosage for the shortest duration of time consistent with individual patient treatment goals [see WARNINGS].Because the risk of overdose increases as opioid doses increase, reserve titration to higher doses of levorphanol tartrate tablets for patients in whom lower doses are insufficiently effective and in whom the expected benefits of using a higher dose opioid clearly outweigh the substantial risks.

Many acute pain conditions (e.g., the pain that occurs with a number of surgical procedures or acute musculoskeletal injuries) require no more than a few days of an opioid analgesic. Clinical guidelines on opioid prescribing for some acute pain conditions are available.

There is variability in the opioid analgesic dose and duration needed to adequately manage pain due both to the cause of pain and to individual patient factors. Initiate the dosing regimen for each patient individually, taking into account the patient’s underlying cause and severity of pain, prior analgesic treatment and response, and risk factors for addiction, abuse, and misuse [see WARNINGS].

Respiratory depression can occur at any time during opioid therapy, especially when initiating and following dosage increases with levorphanol tartrate tablets. Consider this risk when selecting an initial dose and when making dose adjustments [see WARNINGS] .

Patient Access to an Opioid Overdose Reversal Agentfor the Emergency Treatment of Opioid Overdose

Inform patients and caregivers about opioid overdose reversal agents (e.g., naloxone, nalmefene). Discuss the importance of having access to an opioid overdose reversal agent, especially if the patient has risk factors for overdose (e.g., concomitant use of CNS depressants, a history of opioid use disorder, or prior opioid overdose) or if there are household members (including children) or other close contacts at risk for accidental ingestion or opioid overdose. The presence of risk factors for overdose should not prevent the management of pain in any patient [see WARNINGS; Addiction, Abuse, and Misuse; Life-Threatening Respiratory Depression; Risks from Concomitant Use with Benzodiazepines or Other CNS Depressants].
Discuss the options for obtaining an opioid overdose reversal agent (e.g., prescription, over-the-counter, or as part of a community-based program).
There are important differences among the opioid overdose reversal agents, such as route of administration, product strength, approved patient age range, and pharmacokinetics. Be familiar with these differences, as outlined in the approved labeling for those products, prior to recommending or prescribing such an agent.

Initial Dosage

Use of Levorphanol Tartrate Tablets as the First Opioid Analgesic

Initiate treatment with levorphanol tartrate tabletsin a dosing range of 1 to 2 mg every 6 to 8 hours as needed for pain, at the lowest dose necessary to achieve adequate analgesia, provided the patient is assessed for signs of hypoventilation and excessive sedation. Titrate the dose based upon the individual patient’s response to their initial dose of levorphanol tartrate tablets. If necessary, the dose may be increased to up to 3 mg every 6 to 8 hours, after adequate evaluation of the patient's response. Higher doses may be appropriate in opioid tolerant patients. Dosage should be adjusted according to the severity of the pain; age, weight and physical status of the patient; the patient's underlying diseases; use of concomitant medications; and other factors [see INDIVIDUALIZATION OF DOSAGE, WARNINGS AND PRECAUTIONS].

Conversion from Other Opioids to Levorphanol Tartrate Tablets

There is inter-patient variability in the potency of opioid drugs and opioid formulations. Therefore, a conservative approach is advised when determining the total daily dosage of levorphanol tartrate tablets. It is safer to underestimate a patient's 24-hour levorphanol tartrate tablets dosage than to overestimate the 24-hour levorphanol tartrate tablets dosage and manage an adverse reaction due to overdose.

The dosage of levorphanol in patients with cancer or with other conditions for which chronic opioid therapy is indicated must be individualized. Levorphanol is 4 to 8 times as potent as morphine and has a longer half-life. Because there is incomplete cross-tolerance among opioids, when converting a patient from morphine to levorphanol, the total dailydose of levorphanol should begin at approximately 1/15 to 1/12 of the total dailydose of oral morphine that such patients had previously required and then the dose should be adjusted to the patient's clinical response. If a patient is to be placed on fixed-schedule dosing (round-the-clock) with this drug, care should be taken to allow adequate time after each dose change (approximately 72 hours) for the patient to reach a new steady-state before a subsequent dose adjustment to avoid excessive sedation due to drug accumulation.

Note: As with all controlled substances, abuse by health care personnel is possible and the drug should be handled accordingly.

Geriatric Patients

Elderly patients (aged 65 years or older) may have increased sensitivity to levorphanol. In general, use caution when selecting a dosage for an elderly patient, usually starting at the low end of the dosing range, reflecting the greater frequency of decreased hepatic, renal, or cardiac function and of concomitant disease or other drug therapy. The initial dose of levorphanol tartrate tablets should be reduced by 50% or more in the infirm elderly patient [see PRECAUTIONS].

Titration and Maintenance of Therapy

Individually titrate the dose of levorphanol tartrate tablets that provides adequate analgesia and minimizes adverse reactions. Continually reevaluate patients receiving levorphanol tartrate tablets to assess the maintenance of pain control , signs and symptoms of opioid withdrawal, and other adverse reactions, as well as to reassess for the development of addiction, abuse, or misuse [see WARNINGS].

Frequent communication is important among the prescriber, other members of the healthcare team, the patient, and the caregiver/family during periods of changing analgesic requirements, including initial titration.

If a patient is to be placed on fixed-schedule dosing (round-the-clock) with this drug, care should be taken to allow adequate time after each dose change (approximately 72 hours) for the patient to reach a new steady state before a subsequent dose adjustment to avoid excessive sedation due to drug accumulation.

If the level of pain increases after dosage stabilization, attempt to identify the source of increased pain before increasing levorphanol tartrate tablets dosage. If after increasing the dosage, unacceptable opioid- related adverse reactions are observed (including an increase in pain after dosage increase), consider reducing the dosage [see WARNINGS]. Adjust the dosage to obtain an appropriate balance between management of pain and opioid-related adverse reactions.

Levorphanol has a long half-life. The duration of pain relief after a single dose cannot always be predicted from pharmacokinetic principles, and the inter-dose interval may have to be adjusted to suit the patient's individual pharmacodynamic response.

Safe Reduction or Discontinuation of Levorphanol Tartrate Tablets

Do not rapidly reduce or discontinue levorphanol tartrate tablets in patients who may be physically dependent on opioids. Rapid reduction or abrupt discontinuation of opioid analgesics in patients who are physically dependent on opioids has resulted in serious withdrawal symptoms, uncontrolled pain, and suicide. Rapid reduction or abrupt discontinuation has also been associated with attempts to find other sources of opioid analgesics, which may be confused with drug-seeking for abuse. Patients may also attempt to treat their pain or withdrawal symptoms with illicit opioids, such as heroin, and other substances.

When a decision has been made to decrease the dose or discontinue therapy in an opioid-dependent patient taking levorphanol tartrate tablets, there are a variety of factors that should be considered, including the total daily dose of opioid (including levorphanol tartrate tablets) the patient has been taking, the duration of treatment, the type of pain being treated, and the physical and psychological attributes of the patient. It is important to ensure ongoing care of the patient and to agree on an appropriate tapering schedule and follow-up plan so that patient and provider goals and expectations are clear and realistic. When opioid analgesics are being discontinued due to a suspected substance use disorder, evaluate and treat the patient, or refer for evaluation and treatment of the substance use disorder. Treatment should include evidence-based approaches, such as medication assisted treatment of opioid use disorder. Complex patients with co-morbid pain and substance use disorders may benefit from referral to a specialist.

There are no standard opioid tapering schedules that are suitable for all patients. Good clinical practice dictates a patient-specific plan to taper the dose of the opioid gradually. For patients on levorphanol tartrate tablets who are physically opioid-dependent, initiate the taper by a small enough increment (e.g., no greater than 10% to 25% of the total daily dose) to avoid withdrawal symptoms, and proceed with dose- lowering at an interval of every 2 to 4 weeks. Patients who have been taking opioids for briefer periods of time may tolerate a more rapid taper.

It may be necessary to provide the patient with lower dosage strengths to accomplish a successful taper. Reassess the patient frequently to manage pain and withdrawal symptoms, should they emerge. Common withdrawal symptoms include restlessness, lacrimation, rhinorrhea, yawning, perspiration, chills, myalgia, and mydriasis. Other signs and symptoms also may develop, including irritability, anxiety, backache, joint pain, weakness, abdominal cramps, insomnia, nausea, anorexia, vomiting, diarrhea, or increased blood pressure, respiratory rate, or heart rate. If withdrawal symptoms arise, it may be necessary to pause the taper for a period of time or raise the dose of the opioid analgesic to the previous dose, and then proceed with a slower taper. In addition, evaluate patients for any changes in mood, emergence of suicidal thoughts, or use of other substances.

When managing patients taking opioid analgesics, particularly those who have been treated for an extended period of time and/or with high doses for chronic pain, ensure that a multimodal approach to pain management, including mental health support (if needed), is in place prior to initiating an opioid analgesic taper. A multimodal approach to pain management may optimize the treatment of chronic pain, as well as assist with the successful tapering of the opioid analgesic [see WARNINGS, Withdrawal, DRUG ABUSE AND DEPENDENCE].

HOW SUPPLIED

Levorphanol Tartrate Tablets, USP

Dosage Strength | Tablet Color | Tablet Shape | Tablet Debossing | Tablet Scored | NDC Number | Pack Size
2 mg | White to off-white | Flat face beveled edge | Bisect scored on one side and debossed with “762” on other side | Yes | 57664-762-88 | Bottles of 100
3 mg | White to off-white | Oval | Debossed with “058” on one side | No | 57664-058-88 | Bottles of 100

Store at 20° to 25°C (68° to 77°F). [See USP Controlled Room Temperature.]

Dispense in a tight, light-resistant container as defined in the USP with a child-resistant closure.

Store levorphanol tartrate tablets securely and dispose of properly [see PRECAUTIONS, Information for Patients/Caregivers].

Manufactured by:

Ohm Laboratories Inc.

New Brunswick, NJ

Distributed by:

Sun Pharmaceutical Industries, Inc.,

Cranbury, NJ 08512

Iss. 01/2026

5269277

Medication Guide

Levorphanol Tartrate (lee vor' fa nol tar' trate) Tablets USP, CII

Levorphanol tartrate tablets are:

- A strong prescription pain medicine that contains an opioid (narcotic) that is used to manage pain, severe enough to require an opioid pain medicine when other pain treatments such as non-opioid pain medicines do not treat your pain well enough or you cannot tolerate them.
- An opioid pain medicine that can put you at risk for overdose and death. Even if you take your dose correctly as prescribed you are at risk for opioid addiction, abuse, and misuse that can lead to death.

Important information about levorphanol tartrate tablets:

- Get emergency help or call 911 right away if you take too much levorphanol tartrate tablets (overdose). When you first start taking levorphanol tartrate tablets, when your dose is changed, or if you take too much (overdose), serious or life-threatening breathing problems that can lead to death may occur. Ask your healthcare provider about medicines like naloxone or nalmefene that can be used in an emergency to reverse an opioid overdose.
- Taking levorphanol tartrate tablets with other opioid medicines, benzodiazepines, gabapentinoids (gabapentin or pregabalin),alcohol, or other central nervous system depressants (including street drugs) can cause severe drowsiness, decreased awareness, breathing problems, coma and death.
- Never give anyone else your levorphanol tartrate tablets. They could die from taking it. Selling or giving away levorphanol tartrate tablets is against the law.
- Store levorphanol tartrate tablets securely, out of sight and reach of children, and in a location not accessible by others, including visitors to the home.

Do not take levorphanol tartrate tablets if you have:

- severe asthma trouble breathing, or other lung problems
- a bowel blockage or have narrowing of the stomach or intestines.
- previously had an allergic reaction to levorphanol.

Before taking levorphanol tartrate tablets, tell your healthcare provider if you have a history of:

- head injury, seizures
- liver, kidney, thyroid problems
- problems urinating
- pancreas or gallbladder problems
- abuse of street or prescription drugs, alcohol addiction, opioid overdose, or mental health problems.

Tell your healthcare provider if you are:

- noticing your pain getting worse.If your pain gets worse after you take levorphanol tartrate tablets, do not take more of levorphanol tartrate tablets without first talking to your healthcare provider. Talk to your healthcare provider if the pain that you have increases, if you feel more sensitive to pain, or if you have new pain after taking levorphanol tartrate tablets.
- pregnant or planning to become pregnant.Use of levorphanol tartrate tablets for an extended period of time during pregnancy can cause withdrawal symptoms in your newborn baby that could be life-threatening if not recognized and treated.
- breastfeeding.Levorphanol passes into breast milk and may harm your baby. Carefully observe infants for increased sleepiness (more than usual), breathing difficulties, or limpness. Seek immediate medical care if you notice these signs.
- living in a household where there are small children or someone who has abused street or prescription drugs.
- taking prescription or over-the-counter medicines, vitamins, or herbal supplements. Taking levorphanol tartrate tablets with certain other medicines can cause serious side effects that could lead to death.

When taking levorphanol tartrate tablets:

- Do not change your dose. Take levorphanol tartrate tablets exactly as prescribed by your healthcare provider. Use the lowest dose possible for the shortest time needed.
- For acute (short-term) pain, you may only need to take levorphanol tartrate tablets for a few days. You may have some levorphanol tartrate tablets left over that you do not use. See disposal information at the bottom of this section for directions on how to safely throw away (dispose of) your unused levorphanol tartrate tablets.
- Take your prescribed dose every 6 to 8 hours as needed for pain. Do not take more than your prescribed dose. If you miss a dose, take your next dose at your usual time.
- Call your healthcare provider if the dose you are taking does not control your pain.
- If you have been taking levorphanol tartrate tablets regularly, do not stop taking without talking to your healthcare provider.
- Dispose of expired, unwanted, or unused levorphanol tartrate tablets by promptly flushing down the toilet if a drug take-back option is not readily available. Visit www.fda.gov/drugdisposal for additional information on disposal of unused medicines.

While taking levorphanol tartrate tablets DO NOT:

- Drive or operate heavy machinery, until you know how levorphanol tartrate tablets affects you. Levorphanol tartrate tablets can make you sleepy, dizzy, or lightheaded.
- Drink alcohol or use prescription or over-the-counter medicines that contain alcohol. Using products containing alcohol during treatment with levorphanol tartrate tablets may cause you to overdose and die.

The possible side effects of levorphanol tartrate tablets:

- constipation, nausea, sleepiness, vomiting, tiredness, headache, dizziness, abdominal pain. Call your healthcare provider if you have any of these symptoms and they are severe.

Get emergency medical help or call 911 right away if you have:

- trouble breathing, shortness of breath, fast heartbeat, chest pain, swelling of your face, tongue, or throat, extreme drowsiness, light-headedness when changing positions, feeling faint, agitation, high body temperature, trouble walking, stiff muscles, or mental changes such as confusion.
- These are not all the possible side effects of levorphanol tartrate tablets. Call your healthcare provider for medical advice about side effects. You may report side effects to FDA at 1-800-FDA-1088. For more information go to dailymed.nlm.nih.gov.

Manufactured by:

Ohm Laboratories Inc.

New Brunswick, NJ

Distributed by:

Sun Pharmaceutical Industries, Inc.,

Cranbury, NJ 08512

call 1-800-406-7984

This Medication Guide has been approved by the U.S. Food and Drug Administration.

Iss. 01/2026